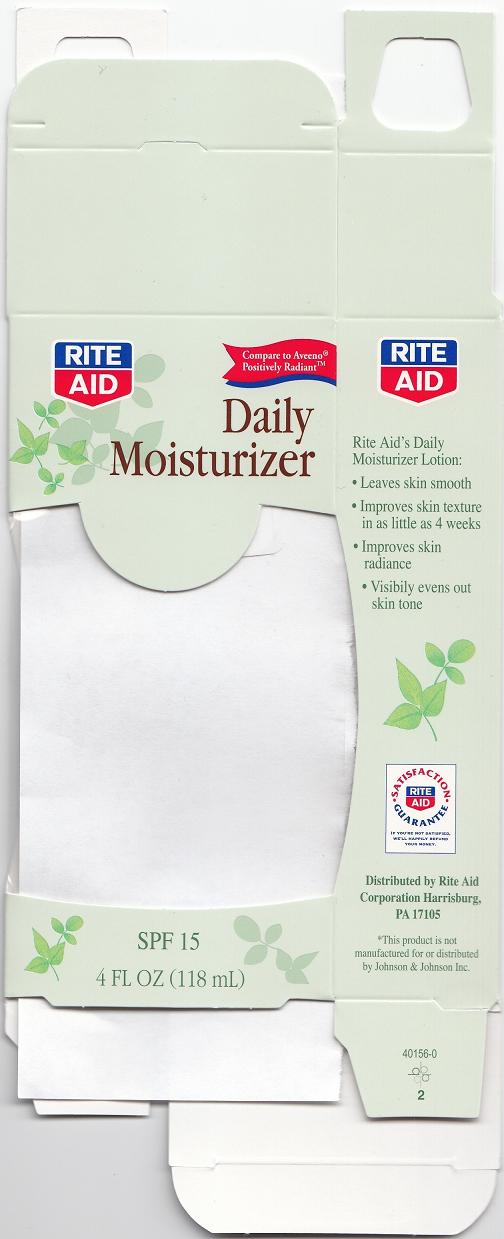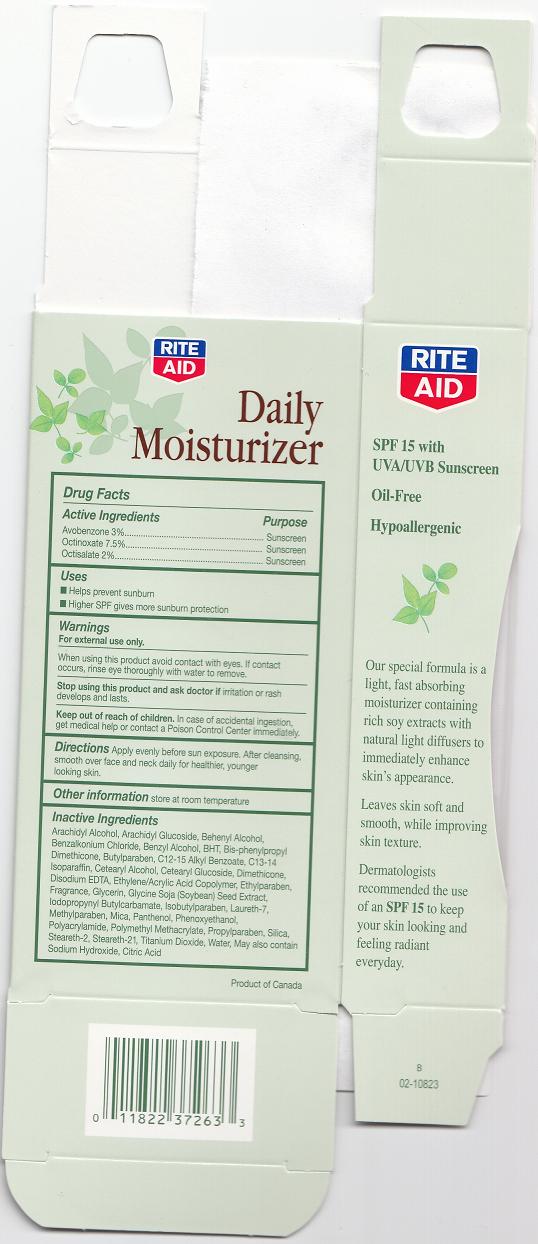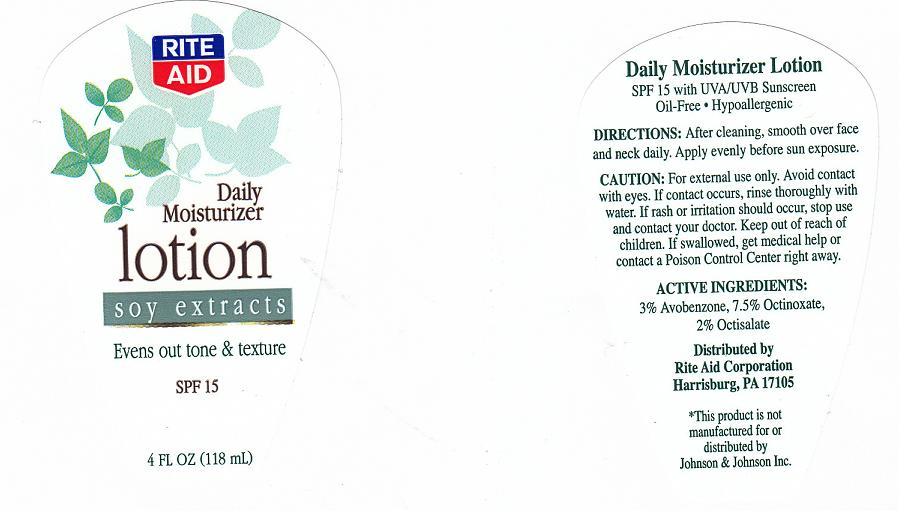 DRUG LABEL: RITE AID DAILY MOISTURIZER
NDC: 11822-6010 | Form: LOTION
Manufacturer: Rite Aid Corporation
Category: otc | Type: HUMAN OTC DRUG LABEL
Date: 20100804

ACTIVE INGREDIENTS: AVOBENZONE 3 mL/100 mL; OCTINOXATE 7.5 mL/100 mL; OCTISALATE 2 mL/100 mL
INACTIVE INGREDIENTS: ARACHIDYL ALCOHOL; DOCOSANOL; BENZALKONIUM CHLORIDE; BENZYL ALCOHOL; BUTYLATED HYDROXYTOLUENE; BUTYLPARABEN; C12-15 ALKYL BENZOATE; C13-14 ISOPARAFFIN; DIMETHICONE; EDETATE DISODIUM; ETHYLPARABEN; GLYCERIN; SOYBEAN; ISOBUTYLPARABEN; LAURETH-7; METHYLPARABEN; MICA; PANTHENOL; PHENOXYETHANOL; PROPYLPARABEN; SILICON DIOXIDE; LAURETH-2; TITANIUM DIOXIDE; WATER; SODIUM HYDROXIDE; CITRIC ACID MONOHYDRATE

DRUG FACTS BOX

ACTIVE INGREDIENTS

- AVOBENZONE 3%
- OCTINOXATE 7.5%
- OCTISALATE 2%

Purpose

Sunscreen

WARNINGS

- FOR EXTERNAL USE ONLY.

WHEN USING THIS PRODUCT

AVOID CONTACT WITH EYES. IF CONTACT OCCURS, RINSE EYE THOROUGHLY WITH WATER TO REMOVE.

STOP USE AND ASK A DOCTOR IF

RASH OR REDNESS DEVELOPS AND LASTS.

KEEP OUT OF REACH OF CHILDREN

IN CASE OF ACCIDENTAL INGESTION, GET MEDICAL HELP OR CONTACT A POISON CONTROL CENTER IMMEDIATELY.

OTHER INFORMATION

STORE AT ROOM TEMPERATURE.

USES

- HELPS PREVENT SUNBURN.
- HIGHER SPF GIVES MORE SUNBURN PROTECTION.

DIRECTIONS

APPLY EVENLY BEFORE SUN EXPOSURE. AFTER CLEANSING, SMOOTH OVER FACE AND NECK DAILY FOR HEALTHIER, YOUNGER LOOKING SKIN.

INACTIVE INGREDIENTS

ARACHIDYL ALCOHOL, ARACHIDYL GLUCOSIDE, BEHENYL ALCOHOL, BENZALKONIUM CHLORIDE, BENZYL ALCOHOL, BHT, BIS-PHENYLPROPYL DIMETHICONE, BUTYLPARABEN, C12-15 ALKYL BENZOATE, C13-14 ISOPARAFFIN, CETEARYL ALCOHOL, CETEARYL GLUCOSIDE, DIMETHICONE, DISODIUM EDTA, ETHYLENE/ACRYLIC COPOLYMER, ETHYLPARABEN, FRAGRANCE, GLYCERINE SOJA (SOYBEAN) SEED EXTRACT, IODOPROPYNYL BUTYLCARBAMATE, ISOBUTYLPARABEN, LAURETH-7, METHYLPARABEN, MICA, PANTHENOL, PHENOXYETHANOL, POLYACRYLAMIDE, POLYMETHYL METHACRYLATE, PROPYLPARABEN, SILICA, STEARETH-2, STEARETH-21, TITANIUM DIOXIDE, WATER, SODIUM HYDROXIDE, CITRIC ACID

PACKAGE LABEL AND CARTON

ra.jpg
cra1.jpg
cra2.jpg